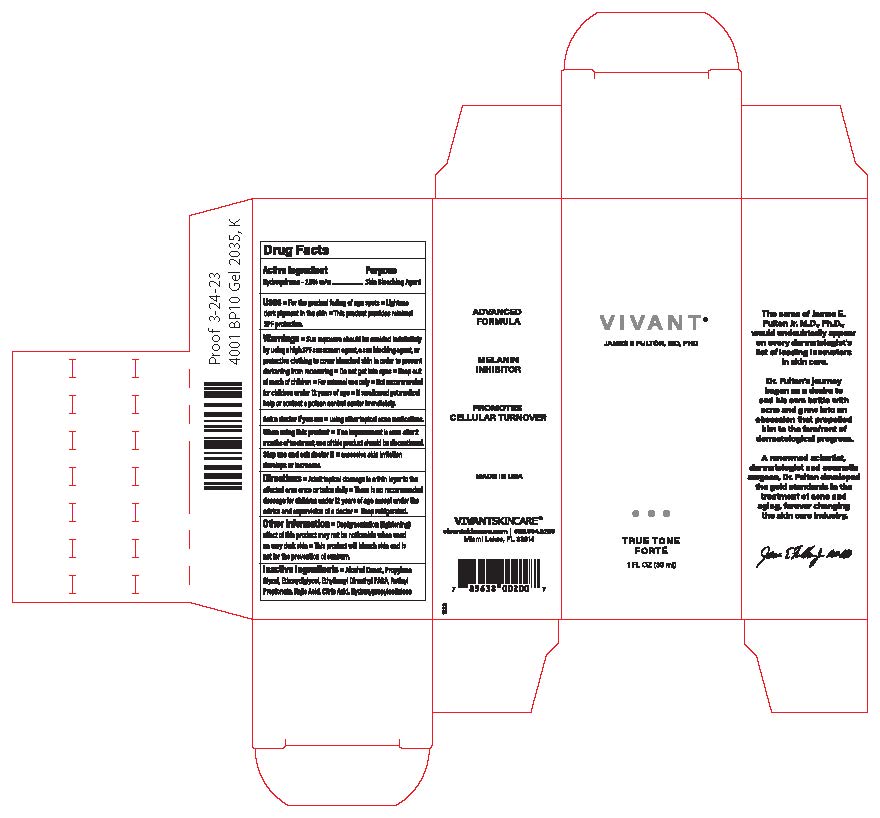 DRUG LABEL: Vivant True Tone Forte
NDC: 63750-001 | Form: GEL
Manufacturer: Vivant Pharmaceuticals, LLC
Category: otc | Type: HUMAN OTC DRUG LABEL
Date: 20250724

ACTIVE INGREDIENTS: HYDROQUINONE 2 g/100 mL
INACTIVE INGREDIENTS: ALCOHOL; DIETHYLENE GLYCOL MONOETHYL ETHER; PADIMATE O; KOJIC ACID; ANHYDROUS CITRIC ACID; RETINYL PROPIONATE; PROPYLENE GLYCOL; LOW-SUBSTITUTED HYDROXYPROPYL CELLULOSE (11% HYDROXYPROPYL; 140000 MW)

Vivant True Tone Forte (Export Only)

Active Ingredient

Hydroquinone (2%)

Indication

Skin Lightening

Uses

■ For the gradual fading of age spots

■ Lightens dark pigment in the skin

■This product provides minimal SPF protection.

Warnings

Warnings ■Sun exposure should be avoided indefinitely by using a high SPF sunscreen agent, a sunblocking agent, or protective clothing to cover bleached skin in order to prevent darkening from reoccurring ■ Do not get into eyes ■Keep out of reach of

children ■For external use only ■Not recommended for children under 12 years of age ■ If swallowed get medical help or contact a poison control center immediately.

Ask a doctor if you are:

using other topical acne medications

Directions

Directions ■ Adult topical dosage is a thin layer to the affected area once or twicedaily■There is no recommended dosage for children under 12 years of age except under the advice and supervision of a doctor ■ Keep refrigerated

Inactive Ingredients

Alcohol Denat, Ethoxydiglycol, Ethylhexyl Dimethyl PABA Hydroquinone USP, Kojic Acid USP, Citric Acid USP, Retinyl Propionate

Propylene Glycol, Hydroxypropylcellulose

When using this product

if not improvement is seen after 2 months of treatment, use of this products should be discontinued

Stop use and ask the doctor if

excessive skin irritation develops or increases

Warnings

Keep out of reach of children■For external only■Not recommended for children under12 years of age